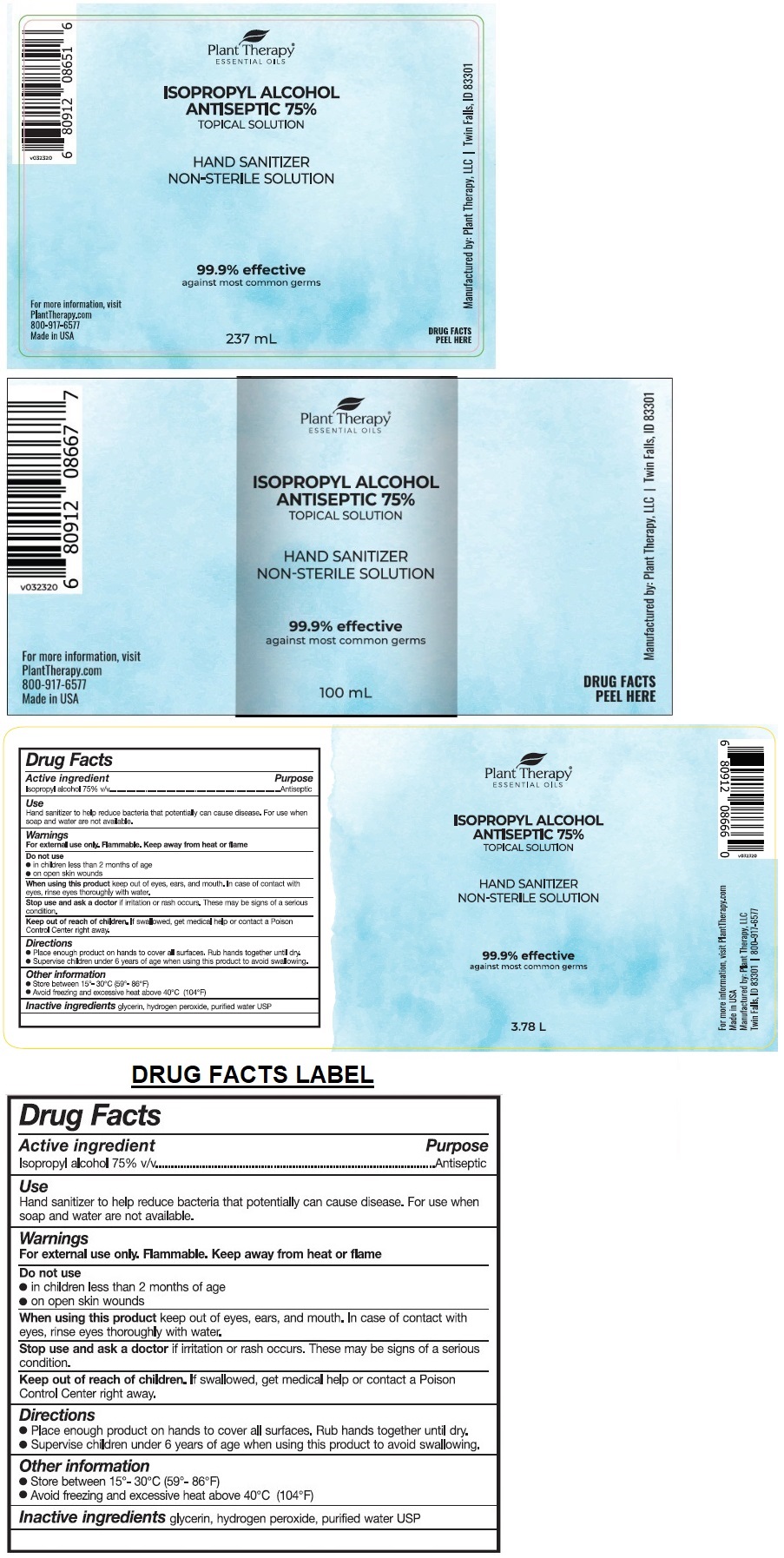 DRUG LABEL: Unscented Hand Sanitizer
NDC: 74877-110 | Form: SPRAY
Manufacturer: Plant Therapy, LLC
Category: otc | Type: HUMAN OTC DRUG LABEL
Date: 20200430

ACTIVE INGREDIENTS: ISOPROPYL ALCOHOL 75 mL/100 mL
INACTIVE INGREDIENTS: GLYCERIN; HYDROGEN PEROXIDE; WATER

Plant Therapy® HAND SANITIZER NON-STERILE SOLUTION

Active ingredient

Isopropyl alcohol 75% v/v

Purpose

Antiseptic

Use

Hand sanitizer to help reduce bacteria that potentially can cause disease. For use when soap and water are not available.

Warnings

For external use only. Flammable. Keep away from heat or flame

Do not use

• in children less than 2 months of age

• on open skin wounds

When using this product keep out of eyes, ears, and mouth. In case of contact with eyes, rinse eyes thoroughly with water.

Stop use and ask a doctor if irritation or rash occurs. These may be signs of a serious condition.

Keep out of reach of children. If swallowed, get medical help or contact a Poison Control Center right away.

Directions

- Place enough product on hands to cover all surfaces. Rub hands together until dry.
- Supervise children under 6 years of age when using this product to avoid swallowing.

Other information

- Store between 15°- 30°C (59°- 86°F)
- Avoid freezing and excessive heat above 40°C (104°F)

Inactive ingredients

glycerin, hydrogen peroxide, purified water USP

ESSENTIAL OILS

TOPICAL SOLUTION

99.9% effective against most common germs

For more information, visit

PlantTherapy.com

800-917-6577

Made in USA

Manufactured by: Plant Therapy, LLC | Twin Falls, ID 83301